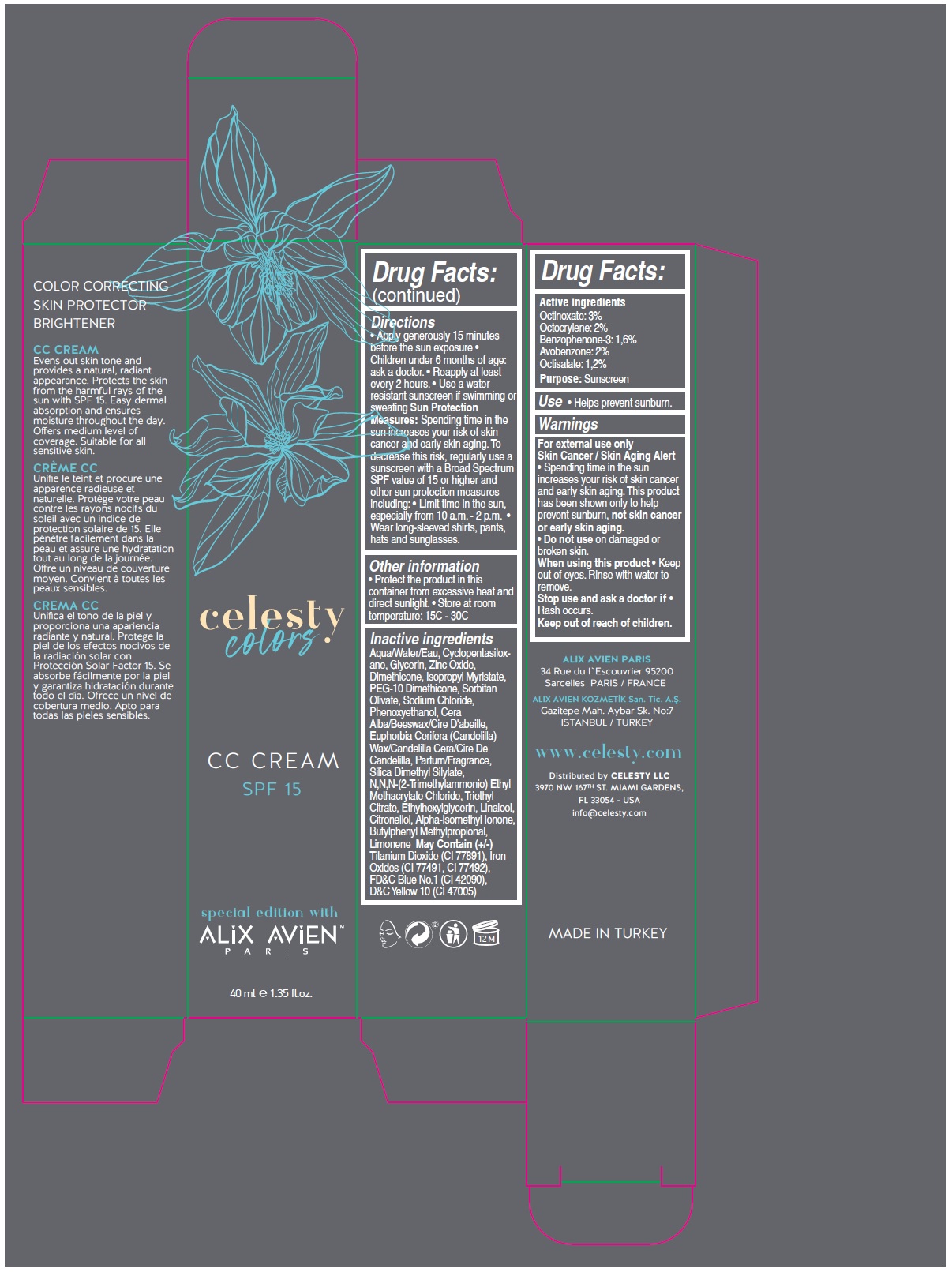 DRUG LABEL: Celesty Colors Special Edition With Alix Avien
NDC: 81120-115 | Form: CREAM
Manufacturer: MABA KOZMETIK LIMITED SIRKETI
Category: otc | Type: HUMAN OTC DRUG LABEL
Date: 20210319

ACTIVE INGREDIENTS: OCTINOXATE 30 mg/1 mL; OCTOCRYLENE 20 mg/1 mL; OXYBENZONE 16 mg/1 mL; AVOBENZONE 20 mg/1 mL; OCTISALATE 12 mg/1 mL
INACTIVE INGREDIENTS: WATER; CYCLOMETHICONE 5; GLYCERIN; ZINC OXIDE; DIMETHICONE; ISOPROPYL MYRISTATE; PEG-10 DIMETHICONE (600 CST); SORBITAN OLIVATE; SODIUM CHLORIDE; PHENOXYETHANOL; YELLOW WAX; CANDELILLA WAX; SILICA DIMETHYL SILYLATE; N,N,N-(2-TRIMETHYLAMMONIO)ETHYL METHACRYLATE CHLORIDE; TRIETHYL CITRATE; ETHYLHEXYLGLYCERIN; LINALOOL, (+/-)-; .BETA.-CITRONELLOL, (R)-; ISOMETHYL-.ALPHA.-IONONE; BUTYLPHENYL METHYLPROPIONAL; LIMONENE, (+)-; TITANIUM DIOXIDE; FERRIC OXIDE RED; FERRIC OXIDE YELLOW; FD&C BLUE NO. 1; D&C YELLOW NO. 10

Celesty colors special edition with ALIX AVIEN™ CC CREAM SPF 15

Active ingredients

Octinoxate: 3%
Octocrylene: 2%
Benzophenone-3: 1.6%
Avobenzone: 2%
Octisalate: 1.2%

Purpose:

Sunscreen

Use

• Helps prevent sunburn.

Warnings

For external use only

Skin Cancer / Skin Aging Alert
• Spending time in the sun increases your risk of skin cancer and early skin aging. This product has been shown only to help prevent sunburn, not skin cancer or early skin aging.

• Do not use on damaged or broken skin.

When using this product • Keep out of eyes. Rinse with water to remove.

Stop use and ask a doctor if • Rash occurs.

Keep out of reach of children.

Directions

• Apply generously 15 minutes before the sun exposure • Children under 6 months of age: ask a doctor. • Reapply at least every 2 hours. • Use a water resistant sunscreen if swimming or sweating Sun Protection Measures: Spending time in the sun increases your risk of skin cancer and early skin aging. To decrease this risk, regularly use a sunscreen with a Broad Spectrum SPF value of 15 or higher and other sun protection measures including: • Limit time in the sun, especially from 10 a.m. - 2 p.m. • Wear long-sleeved shirts, pants, hats and sunglasses.

Other information

• Protect the product in this container from excessive heat and direct sunlight.

• Store at room temperature: 15C - 30C

Inactive ingredients

Aqua/Water/Eau, Cyclopentasiloxane, Glycerin, Zinc Oxide, Dimethicone, Isopropyl Myristate, PEG-10 Dimethicone, Sorbitan Olivate, Sodium Chloride,Phenoxyethanol, Cera Alba/Beeswax/Cire D'abeille, Euphorbia Cerifera (Candelilla) Wax/Candelilla Cera/Cire De Candelilla, Parfum/Fragrance, Silica Dimethyl Silylate, N,N,N-(2-Trimethylammonio) Ethyl Methacrylate Chloride, Triethyl Citrate, Ethylhexylglycerin, Linalool, Citronellol, Alpha-Isomethyl Ionone, Butylphenyl Methylpropional, Limonene May Contain (+/-) Titanium Dioxide (CI 77891), Iron Oxides (CI 77491, CI 77492), FD&C Blue No.1 (CI 42090), D&C Yellow 10 (CI 47005)

CC CREAM

SPF 15

COLOR CORRECTING SKIN PROTECTOR BRIGHTENER

Evens out skin tone and provides a natural, radiant appearance. Protects the skin from the harmful rays of the sun with SPF 15. Easy dermal absorption and ensures moisture throughout the day. Offers medium level of coverage. Suitable for all sensitive skin.

ALIX AVIEN PARIS

34 Rue du l'Escouvrier 95200
Sarcelles PARIS / FRANCE

ALIX AVIEN KOZMETİK San. Tic. A.Ş.

Gazitepe Mah. Aybar Sk. No:7
ISTANBUL / TURKEY

www.celesty.com

Distributed by CELESTY LLC
3970 NW 167TH ST. MIAMI GARDENS,
FL 33054 - USA
info@celesty.com

MADE IN TURKEY